DRUG LABEL: Unknown
Manufacturer: Food and Drug Administration
Category: other | Type: Indexing - Pharmacologic Class
Date: 20140407

APREPITANT Pharmacologic Class Indexing